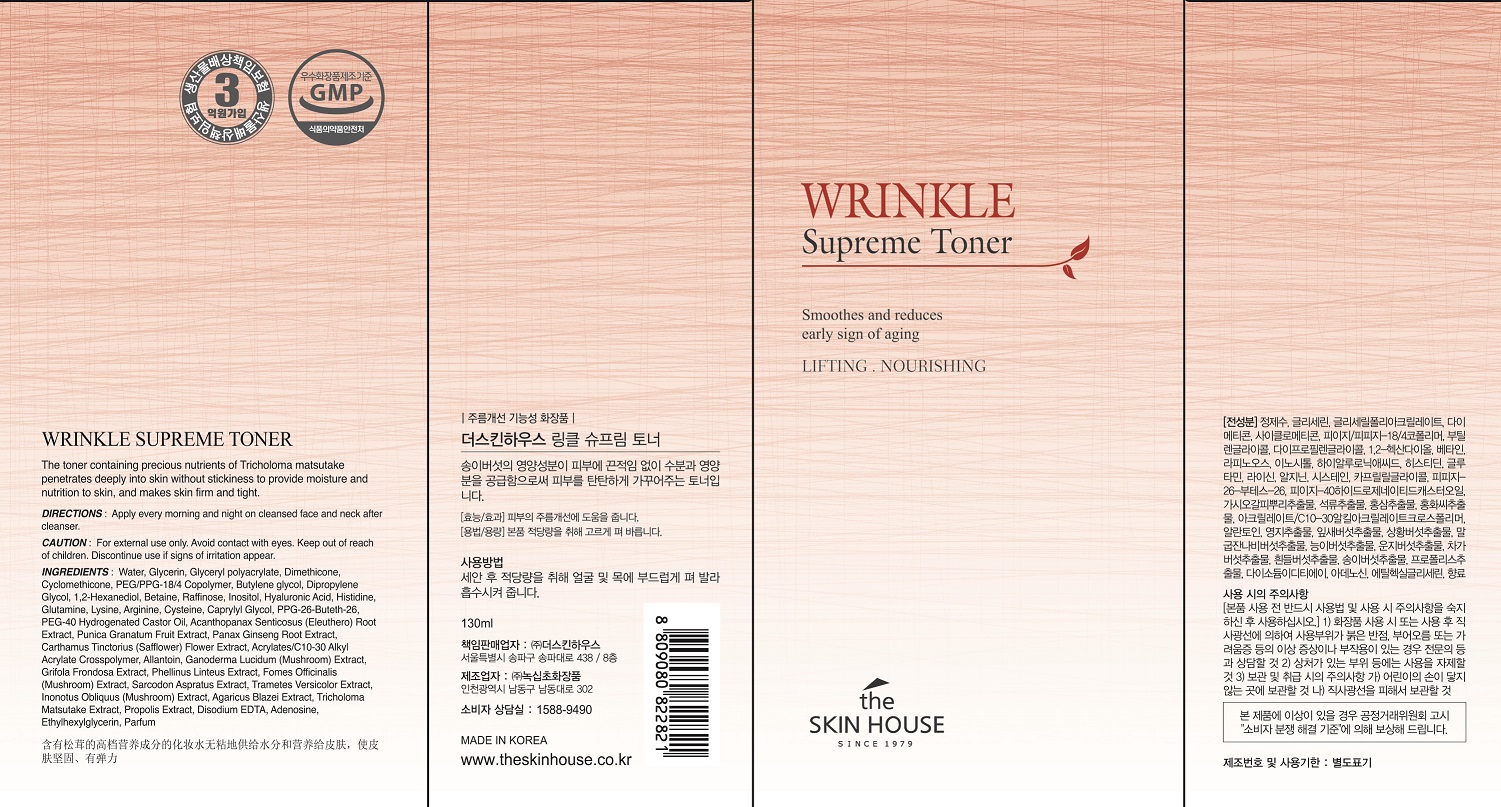 DRUG LABEL: THE SKINHOUSE WRINKLE SUPREME TONER
NDC: 73590-0008 | Form: LIQUID
Manufacturer: NOKSIBCHO cosmetic Co., Ltd.
Category: otc | Type: HUMAN OTC DRUG LABEL
Date: 20200129

ACTIVE INGREDIENTS: ASIAN GINSENG 0.5 g/100 mL
INACTIVE INGREDIENTS: WATER; BUTYLENE GLYCOL

Drug Facts

ACTIVE INGREDIENT

Panax Ginseng Root Extract, Ganoderma Lucidum (Mushroom) Extract, Phellinus Linteus Extract, Inonotus Obliquus (Mushroom) Extract, Agaricus Blazei Extract, Tricholoma Matsutake Extract,Hizikia Fusiforme Extract, Codium Tomentosum Extract, Gelidium Cartilagineum Extract.

INACTIVE INGREDIENT

Water
Glycerin
Glyceryl polyacrylate
Dimethicone
Cyclomethicone
PEG/PPG-18/4 Copolymer
Butylene glycol
Dipropylene Glycol
1,2-Hexanediol
Betaine
Water
Butylene glycol
Betaine
Raffinose
Inositol
Hyaluronic Acid
Histidine
Glutamine
Glycerin
Lysine
Arginine
Cysteine
1,2-Hexanediol
Caprylyl Glycol
PPG-26-Buteth-26
PEG-40 Hydrogenated Castor Oil
Acanthopanax Senticosus (Eleuthero) Root Extract
Punica Granatum Fruit Extract
Panax Ginseng Root Extract
Carthamus Tinctorius (Safflower) Flower Extract
Panax Ginseng Root Extract
Acrylates/C10-30 Alkyl Acrylate Crosspolymer
Arginine
Allantoin
Ganoderma Lucidum (Mushroom) Extract
Grifola Frondosa Extract
Phellinus Linteus Extract
Fomes Officinalis (Mushroom) Extract
Sarcodon Aspratus Extract
Trametes Versicolor Extract
Inonotus Obliquus (Mushroom) Extract
Agaricus Blazei Extract
Tricholoma Matsutake Extract
Propolis Extract
Disodium EDTA
Adenosine
Ethylhexylglycerin
Parfum

PURPOSE

-Anti-wrinkle function toner

The toner contains various nutrition which is good for skin care and antioxidant such as panax ginseng root extract and 9 types of mushroom. Transparent viscous toner will supply nutrition to skin and be absorbed completely to make skin shiny.

It is a nutrition supply toner which helps recovery of skin fatigue and replenishment of skin basic nutrition as if essence was applied to skin.

keep out of reach of the children

INDICATIONS AND USAGE

After cleansing, wet a cotton pad with enough toner and apply it on your face.

Apply it softly from the center part of your face to the outer part along the skin texture.

Pat your face to be absorbed completely.

WARNINGS

For external use only
When using this product

■ if the following symptoms occurs after use, stop use and consult with a skin specialist

red specks, swelling, itching

■ don’t use on the part where there is injury, eczema, or dermatitis

Keep out of reach of children

■ if swallowed, get medical help or contact a person control center immediately

DOSAGE AND ADMINISTRATION

for external use only